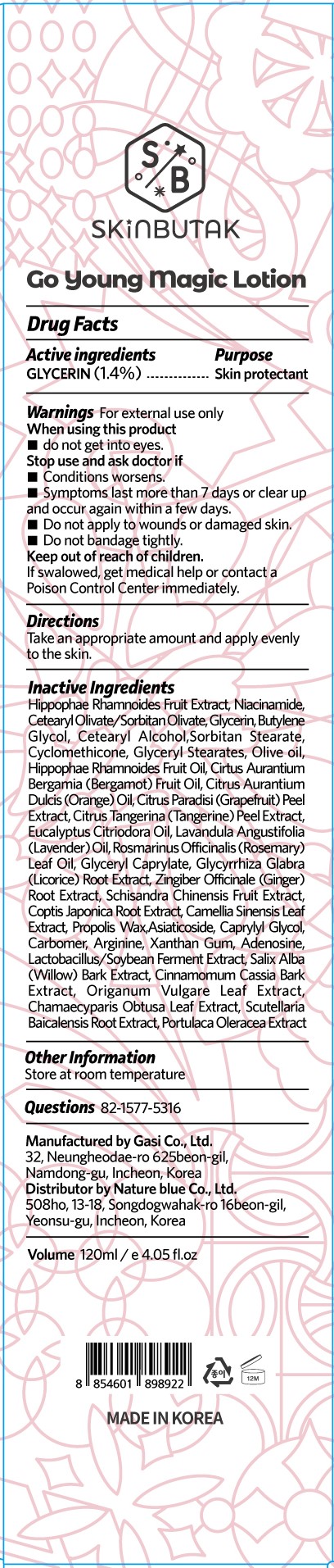 DRUG LABEL: SKINBUTAK GO YOUNG MAGICLOTION
NDC: 81851-201 | Form: LOTION
Manufacturer: NatureBlue Co.,Ltd
Category: otc | Type: HUMAN OTC DRUG LABEL
Date: 20210426

ACTIVE INGREDIENTS: GLYCERIN 1.4 mg/100 mL
INACTIVE INGREDIENTS: ORANGE OIL, COLD PRESSED; GINGER; GREEN TEA LEAF; CARBOMER HOMOPOLYMER, UNSPECIFIED TYPE; ARGININE; XANTHAN GUM; SALIX ALBA BARK; OREGANO; CHAMAECYPARIS OBTUSA LEAF; SCUTELLARIA BAICALENSIS ROOT; HIPPOPHAE RHAMNOIDES FRUIT; CETEARYL OLIVATE; HIPPOPHAE RHAMNOIDES FRUIT OIL; CHINESE CINNAMON; PURSLANE; NIACINAMIDE; ASIATICOSIDE; BUTYLENE GLYCOL; CETOSTEARYL ALCOHOL; CYCLOMETHICONE; OLIVE OIL; BERGAMOT OIL; CORYMBIA CITRIODORA LEAF OIL; LAVENDER OIL; GLYCERYL MONOCAPRYLATE; GLYCYRRHIZA GLABRA; PROPOLIS WAX; SCHISANDRA CHINENSIS FRUIT; COPTIS JAPONICA ROOT; CAPRYLYL GLYCOL; SORBITAN MONOSTEARATE; GLYCERYL MONOSTEARATE; GRAPEFRUIT PEEL; TANGERINE PEEL; ROSEMARY OIL; ADENOSINE

81851-201 SKINBUTAK GO YOUNG MAGIC LOTION

Active ingredients

GLYCERIN

Purpose

Skin protectant

Use

For soft, brighter, and revitalized skin

Warnings

For external use only.

If swalowed, get medical help or contact a Poison Control Center immediately.

When using this product

- do not get into eyes.

Stop use and ask doctor if

- Conditions worsens.
- Symptoms last more than 7 days or clear up and occur again within a few days.
- Do not apply to wounds or damaged skin.
- Do not bandage tightly.

Keep out of reach of children.

Directions

Take an appropriate amount and apply evenly to the skin.

Inactive Ingredients

Hippophae Rhamnoides Fruit Extract, Niacinamide, Cetearyl Olivate/Sorbitan Olivate, Glycerin, Butylene Glycol, Cetearyl Alcohol,Sorbitan Stearate, Cyclomethicone, Glyceryl Stearates, Olive oil, Hippophae Rhamnoides Fruit Oil, Cirtus Aurantium Bergamia (Bergamot) Fruit Oil, Citrus Aurantium Dulcis (Orange) Oil, Citrus Paradisi (Grapefruit) Peel Extract, Citrus Tangerina (Tangerine) Peel Extract, Eucalyptus Citriodora Oil, Lavandula Angustifolia (Lavender) Oil, Rosmarinus Officinalis (Rosemary) Leaf Oil, Glyceryl Caprylate, Glycyrrhiza Glabra (Licorice) Root Extract, Zingiber Officinale (Ginger) Root Extract, Schisandra Chinensis Fruit Extract, Coptis Japonica Root Extract, Camellia Sinensis Leaf Extract, Propolis Wax,Asiaticoside, Caprylyl Glycol, Carbomer, Arginine, Xanthan Gum, Adenosine, Lactobacillus/Soybean Ferment Extract, Salix Alba (Willow) Bark Extract, Cinnamomum Cassia Bark Extract, Origanum Vulgare Leaf Extract, Chamaecyparis Obtusa Leaf Extract, Scutellaria Baicalensis Root Extract, Portulaca Oleracea Extract

Other Information

Store at room temperature